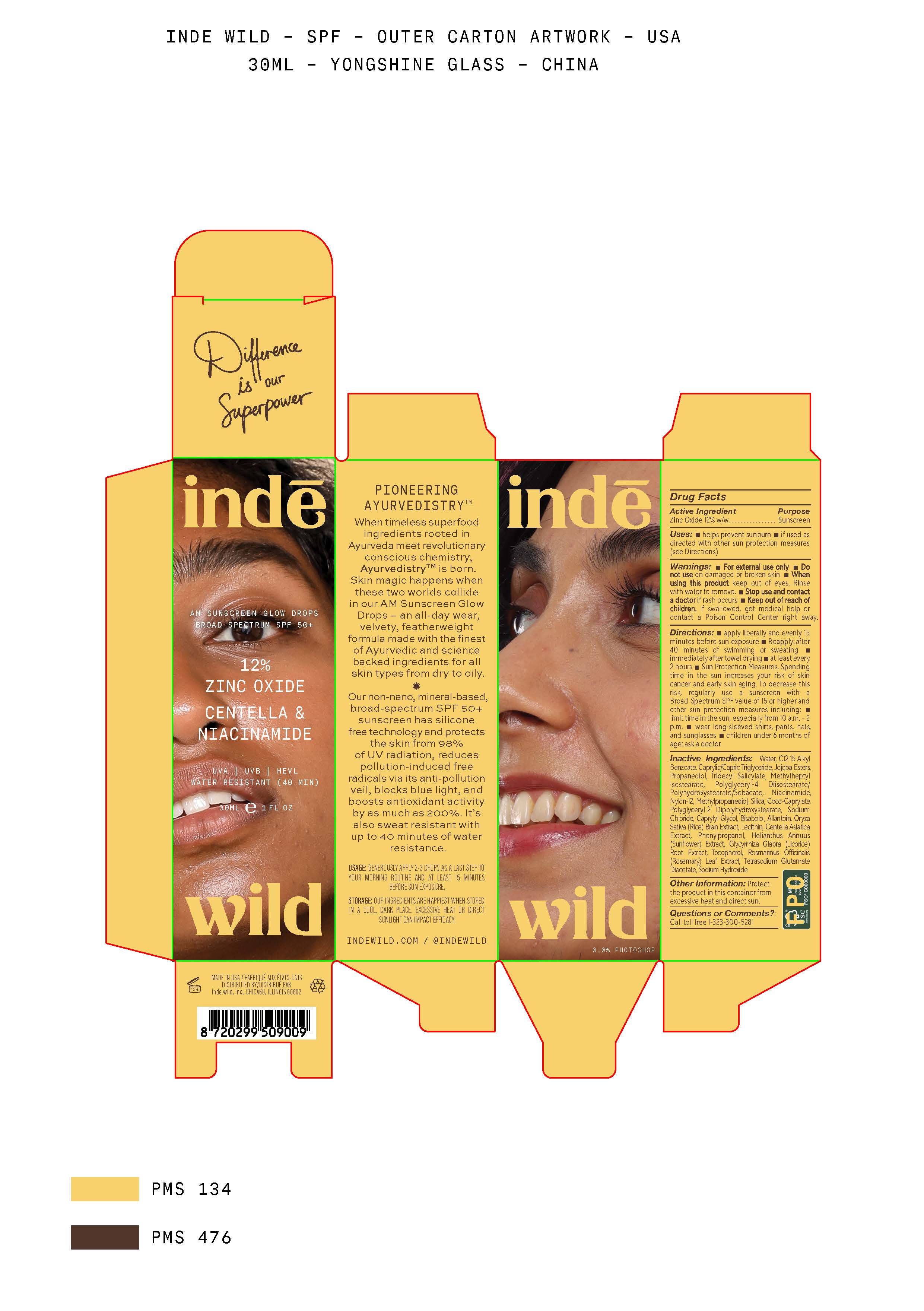 DRUG LABEL: Inde Wild
NDC: 83054-1502 | Form: LOTION
Manufacturer: Inde Wild
Category: otc | Type: HUMAN OTC DRUG LABEL
Date: 20251106

ACTIVE INGREDIENTS: ZINC OXIDE 132 mg/1 mL
INACTIVE INGREDIENTS: ORYZA SATIVA WHOLE; TRIDECYL SALICYLATE; SILICON DIOXIDE; TOCOPHEROL; CAPRYLYL GLYCOL; COCO-CAPRYLATE; NYLON-12; PHENYLPROPANOL; HELIANTHUS ANNUUS FLOWERING TOP; LECITHIN, SOYBEAN; METHYLHEPTYL ISOSTEARATE; JOJOBA OIL; METHYLPROPANEDIOL; POLYGLYCERYL-2 DIPOLYHYDROXYSTEARATE; ALLANTOIN; ALKYL (C12-15) BENZOATE; ROSMARINUS OFFICINALIS FLOWER; .ALPHA.-BISABOLOL, (+)-; SODIUM HYDROXIDE; WATER; NIACINAMIDE; PROPANEDIOL; TETRASODIUM GLUTAMATE DIACETATE; SODIUM CHLORIDE; POLYGLYCERYL-4 DIISOSTEARATE/POLYHYDROXYSTEARATE/SEBACATE

Inde Wild